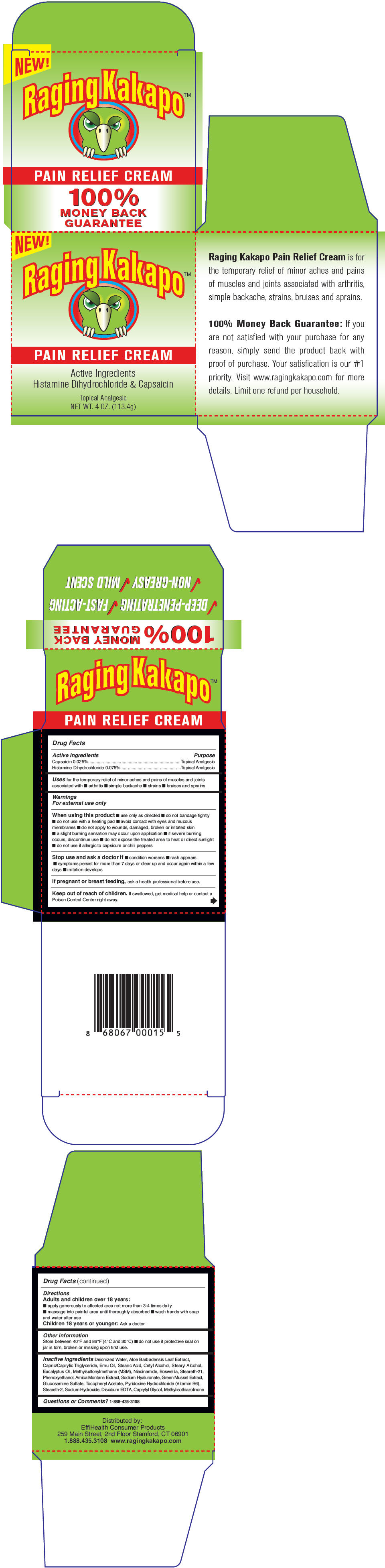 DRUG LABEL: Raging Kakapo Pain Relieve
NDC: 70984-001 | Form: CREAM
Manufacturer: EffiHealth LLC
Category: otc | Type: HUMAN OTC DRUG LABEL
Date: 20171030

ACTIVE INGREDIENTS: CAPSAICIN 0.25 mg/1 g; histamine dihydrochloride 0.75 mg/1 g
INACTIVE INGREDIENTS: water; ALOE VERA LEAF; MEDIUM-CHAIN TRIGLYCERIDES; Emu Oil; Stearic Acid; Cetyl Alcohol; Stearyl Alcohol; Eucalyptus Oil; DIMETHYL SULFONE; Niacinamide; INDIAN FRANKINCENSE; Steareth-21; Phenoxyethanol; ARNICA MONTANA; HYALURONATE SODIUM; Glucosamine Sulfate; .ALPHA.-TOCOPHEROL ACETATE; Pyridoxine Hydrochloride; Steareth-2; Sodium Hydroxide; EDETATE DISODIUM; Caprylyl Glycol; Methylisothiazolinone

Raging Kakapo™ Pain Relieve Cream

Drug Facts

ACTIVE INGREDIENT

Active Ingredients | Purpose
Capsaicin 0.025% | Topical Analgesic
Histamine Dihydrochloride 0.075% | Topical Analgesic

Uses

for the temporary relief of minor aches and pains of muscles and joints associated with

- arthritis
- simple backache
- strains
- bruises and sprains.

Warnings

For external use only

When using this product

- use only as directed
- do not bandage tightly
- do not use with a heating pad
- avoid contact with eyes and mucous membranes
- do not apply to wounds, damaged, broken or irritated skin
- a slight burning sensation may occur upon application
- if severe burning occurs, discontinue use
- do not expose the treated area to heat or direct sunlight
- do not use if allergic to capsicum or chili peppers

Stop use and ask a doctor if

- condition worsens
- rash appears
- symptoms persist for more than 7 days or clear up and occur again within a few days
- irritation develops

PREGNANCY OR BREAST FEEDING

If pregnant or breast feeding, ask a health professional before use.

Keep out of reach of children. If swallowed, get medical help or contact a Poison Control Center right away.

Directions

Adults and children over 18 years

- apply generously to affected area not more than 3-4 times daily
- massage into painful area until thoroughly absorbed
- wash hands with soap and water after use

Children 18 years or younger

Ask a doctor

Other information

Store between 40°F and 86°F (4°C and 30°C)

- do not use if protective seal on jar is torn, broken or missing upon first use.

Inactive ingredients

Deionized Water, Aloe Barbadensis Leaf Extract, Capric/Caprylic Triglyceride, Emu Oil, Stearic Acid, Cetyl Alcohol, Stearyl Alcohol, Eucalyptus Oil, Methylsulfonylmethane (MSM), Niacinamide, Boswellia, Steareth-21, Phenoxyethanol, Arnica Montana Extract, Sodium Hyaluronate, Green Mussel Extract, Glucosamine Sulfate, Tocopheryl Acetate, Pyridoxine Hydrochloride (Vitamin B6), Steareth-2, Sodium Hydroxide, Disodium EDTA, Caprylyl Glycol, Methylisothiazolinone

Questions or Comments?

1-888-435-3108

Distributed by:
EffiHealth Consumer Products
259 Main Street, 2nd Floor Stamford, CT 06901

PRINCIPAL DISPLAY PANEL - 113.4 g Jar Carton

NEW!

Raging Kakapo™

PAIN RELIEF CREAM

Active Ingredients
Histamine Dihydrochloride & Capsaicin

Topical Analgesic
NET WT. 4 OZ. (113.4g)